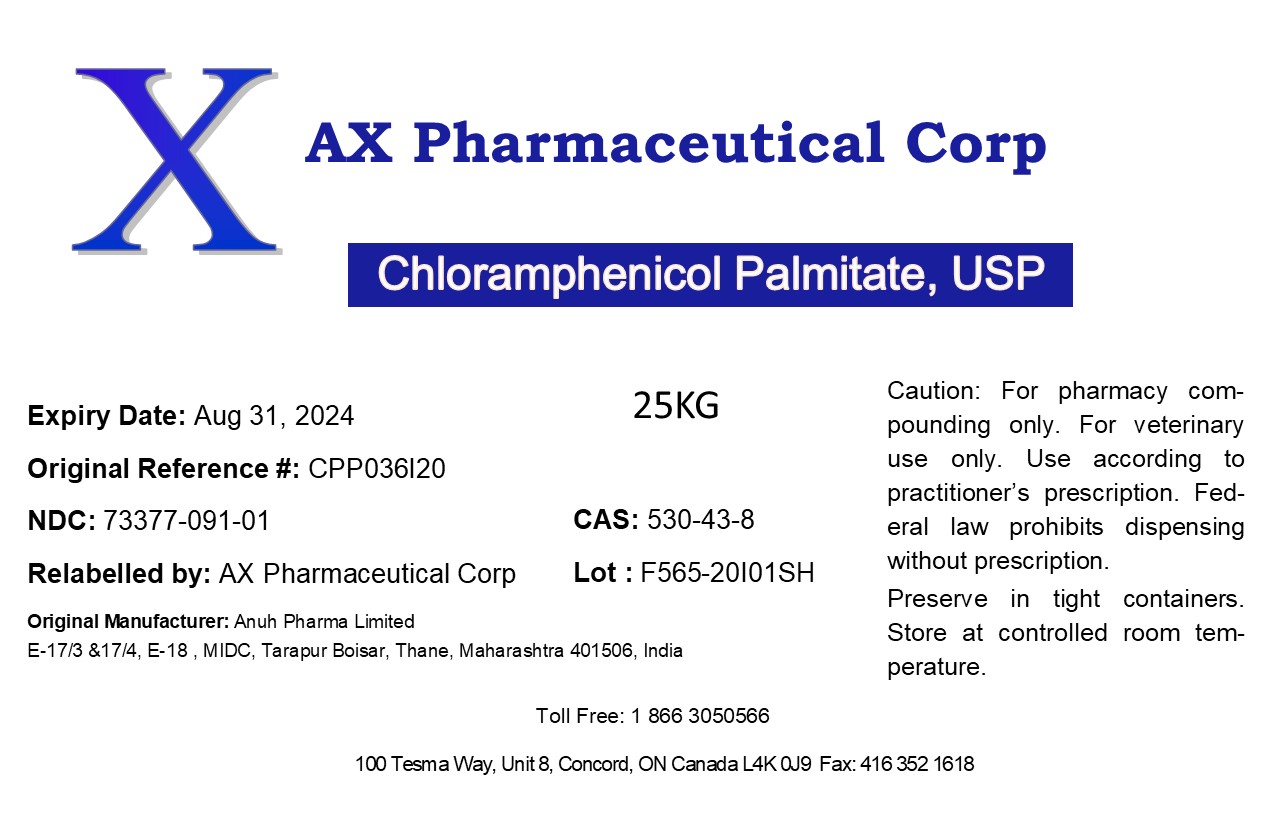 DRUG LABEL: Chloramphenicol Palmitate
NDC: 73377-091 | Form: POWDER
Manufacturer: AX Pharmaceutical Corp
Category: other | Type: BULK INGREDIENT
Date: 20201203

ACTIVE INGREDIENTS: CHLORAMPHENICOL PALMITATE 1 kg/1 kg

Chloramphenicol Palmitate